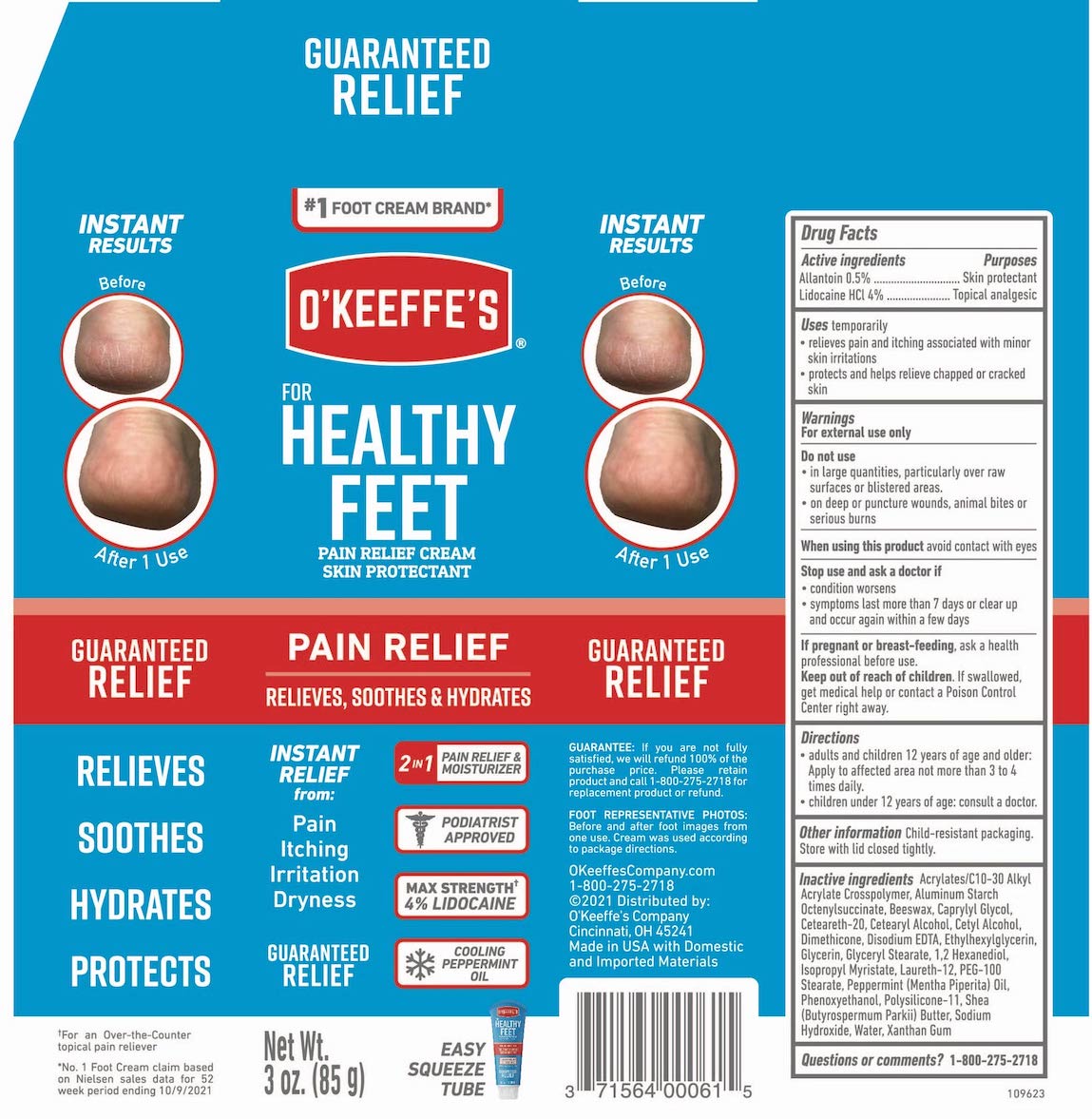 DRUG LABEL: OKeeffes Healthy Feet
NDC: 71564-006 | Form: CREAM
Manufacturer: The Gorilla Glue Company/O'Keeffe's Company
Category: otc | Type: HUMAN OTC DRUG LABEL
Date: 20240101

ACTIVE INGREDIENTS: ALLANTOIN 0.5 g/100 g; LIDOCAINE HYDROCHLORIDE 4 g/100 g
INACTIVE INGREDIENTS: PEPPERMINT OIL; PHENOXYETHANOL; DIMETHICONE/VINYL DIMETHICONE CROSSPOLYMER (SOFT PARTICLE); SHEA BUTTER; SODIUM HYDROXIDE; WATER; XANTHAN GUM; EDETATE DISODIUM ANHYDROUS; ETHYLHEXYLGLYCERIN; GLYCERIN; 1,2-HEXANEDIOL; ISOPROPYL MYRISTATE; WHITE WAX; CAPRYLYL GLYCOL; POLYOXYL 20 CETOSTEARYL ETHER; CETOSTEARYL ALCOHOL; CETYL ALCOHOL; DODECAMETHYLPENTASILOXANE; GLYCERYL 1-STEARATE; CARBOMER INTERPOLYMER TYPE B (ALLYL PENTAERYTHRITOL CROSSLINKED); ALUMINUM STARCH OCTENYLSUCCINATE; LAURETH-12; PEG-100 STEARATE

O"Keeffe's Healthy Feet Pain Relief

Drug Facts

Active ingredients

Allantoin 0.5%

Lidodaine HCl 4%

Purposes

Skin protectant

Topical analgesic

INDICATIONS AND USAGE

Uses temporarily

- relieves pain and itching associated with minor skin irritations
- protects and helps relieve chapped or cracked skin

Warnings

For external use only

Do not use

- in large quantities, particularly over raw surfaces or blistered areas.
- on deep or puncture wounds, animal bites or serious burns

When using this product avoid contact with eyes

Stop use and ask a doctor if

- condition worsens
- symptoms last more than 7 days or clear up and occur again within a few days

PREGNANCY OR BREAST FEEDING

If pregnant or breast-feeding, ask a health professional before use.

Keep out of reach of children. If swallowed, get medical help or contact a Poison Control Center right away.

Directions

- adults and children 12 years of age and older: Apply to affected area not more than 3 to 4 times daily.
- children under 12 years of age: consult a doctor.

Other information

Child-resistant packaging. Store with lid closed tightly.

Inactive ingredients

Acrylates/C10-30 Alkyl Acrylate Crosspolymer, Aluminum Starch Octenylsuccinate, Beeswax, Caprylyl Glycol, Ceteareth-20, Cetearyl Alcohol, Cetyl Alcohol, Dimethicone, Disodium EDTA, Ethylhexylglycerin, Glycerin, Glyceryl Stearate, 1,2 Hexanediol, Isopropyl Myristate, Laureth-12, PEG-100 Stearate, Peppermint (Mentha Piperita) Oil, Phenoxyethanol, Polysilicone-11, Shea (Butyrospermum Parkii) Butter, Sodium Hydroxide, Water, Xanthan Gum

Questions or comments?

1-800-275-2718

GUARANTEED RELIEF

GUARANTEE: If you are not fully satisfied, we will refund 100% of the purchase price. Please retain product and call 1-800-275-2718 for replacement product or refund.

FOOT REPRESENTATIVE PHOTOS: Before and after foot images from one use. Cream was used according to package directions.

O'Keeffe's Company.com

1-800-275-2718

©2021 Distributed by:

O'Keeffe's Company

Cincinnati, OH 45241

Made in the USA with Domestic and Imported Materials

PACKAGE LABEL

O'KEEFFE'S

FOR HEALTHY FEET

PAIN RELIEF CREAM

SKIN PROTECTANT

PAIN RELIEF

RELIEVES, SOOTHES & HYDRATES

INSTANT RELIEF from:

Pain

Itching

Irritation

Dryness

GUARANTEED RELIEF

2 IN 1 PAIN RELIEF & MOISTURIZER

PODIATRIST APPROVED

MAX STRENGTH 4% LIDOCAINE

COOLING PEPPERMINT OIL

Net Wt. 3 oz. (85 g)